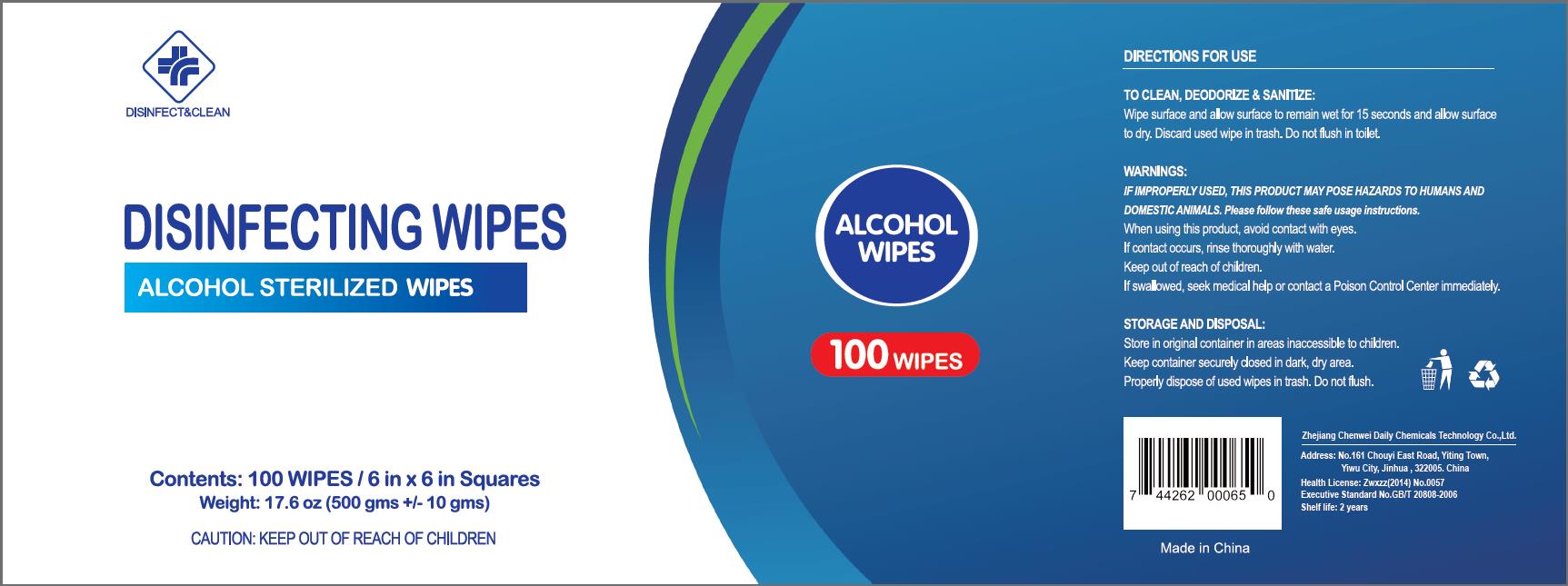 DRUG LABEL: Alcohol sterilized wipes
NDC: 80213-121 | Form: CLOTH
Manufacturer: Zhejiang Chenwei Daily Chemicals Technology Co.,Ltd.
Category: otc | Type: HUMAN OTC DRUG LABEL
Date: 20200825

ACTIVE INGREDIENTS: ALCOHOL 3.3 mL/1 1
INACTIVE INGREDIENTS: WATER; POLYESTER (ADIPIC ACID, 1,6-HEXANEDIOL, NEOPENTYL GLYCOL); DIRECT BLACK 19

ChenWei Wipes Alcohol 75%, 100ct

ACTIVE INGREDIENT(S)

Alcohol: 75% v/v ...... Purpose: Antiseptic

PURPOSE

TO CLEAN, DEODORIZE & SANITIZE

WARNINGS

IF IMPROPERLY USED, THIS PRODUCT MAY POSE HAZARDS TO HUMANS AND DOMESTIC ANIMALS.

Please follow these safe usage instructions.

Do not use

- in children less than 2 months of age
- on open skin wounds

Stop use and ask a doctor

if irritation or rash occurs. These may be signs of a serious condition.

Keep out of reach of children.

If swallowed, seek medical help or contact a Poison Control Center immediately.

INDICATIONS AND USAGE

Wipe surface and allow surface to remain wet for 15 seconds and allow surface to dry. Discard used wipe in trash. Do not flush in toilet.

DOSAGE AND ADMINISTRATION

Wipe surface and allow surface to remain wet for 15 seconds and allow surface to dry. Discard used wipe in trash. Do not flush in toilet.

When using this product, avoid contact with eyes.

If contact occurs, rinse eyes thoroughly with water.

STORAGE AND DISPOSAL

Store in original container in areas inaccessible to children.

Keep container securely closed in dark, dry area.

Properly dispose of used wipes in trash. Do not flush.

INACTIVE INGREDIENT

Water, Polyester, Viscose